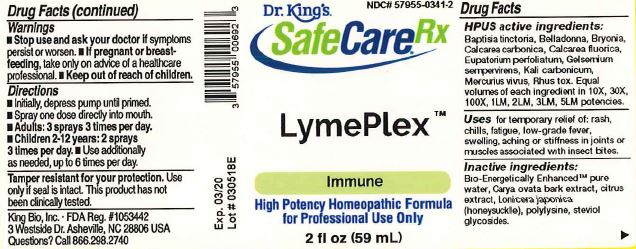 DRUG LABEL: LymePlex
NDC: 57955-0341 | Form: LIQUID
Manufacturer: King Bio Inc.
Category: homeopathic | Type: HUMAN OTC DRUG LABEL
Date: 20180626

ACTIVE INGREDIENTS: BAPTISIA TINCTORIA ROOT 10 [hp_X]/59 mL; ATROPA BELLADONNA 10 [hp_X]/59 mL; BRYONIA ALBA ROOT 10 [hp_X]/59 mL; OYSTER SHELL CALCIUM CARBONATE, CRUDE 10 [hp_X]/59 mL; CALCIUM FLUORIDE 10 [hp_X]/59 mL; EUPATORIUM PERFOLIATUM FLOWERING TOP 10 [hp_X]/59 mL; GELSEMIUM SEMPERVIRENS ROOT 10 [hp_X]/59 mL; POTASSIUM CARBONATE 10 [hp_X]/59 mL; MERCURY 10 [hp_X]/59 mL; TOXICODENDRON PUBESCENS LEAF 10 [hp_X]/59 mL
INACTIVE INGREDIENTS: WATER; CARYA OVATA BARK; CITRUS BIOFLAVONOIDS; LONICERA JAPONICA FLOWER; POLYEPSILON-LYSINE (4000 MW); REBAUDIOSIDE A

LymePlex

ACTIVE INGREDIENT

Drug Facts__________________________________________________________________________________________________________

HPUS active ingredients: Baptisia tinctoria, Belladonna, Bryonia, Calcarea carbonica, Calcarea fluorica, Eupatorium perfoliatum, Gelsemium sempervirens, Kali carbonicum, Mercurius vivus, Rhus toxicodendron. Equal volumes of each ingredient in 10X, 30X, 100X, 1LM, 2LM, 3LM, 5LM potencies.

INDICATIONS AND USAGE

Uses for temporary relief of: rash, chills, fatigue, low-grade fever, swelling, aching or stiffness in joints or muscles associated with insect bites.

Inactive Ingredients:

Bio-Energetically Enhanced™ pure water, Carya ovata bark extract, citrus extract, Lonicera japonica (honeysuckle), polylysine, steviol glycosides.

Warnings

- Stop use and ask your doctor if symptoms persist or worsen.
- If pregnant or breast-feeding, take only on advice of a healthcare professional.

- Keep out of reach of children.

Directions

- Initially, depress pump until primed.
- Spray one dose directly into mouth.
- Adults: 3 sprays 3 times per day.
- Children 2-12 years: 2 sprays 3 times per day.
- Use additionally as needed, up to 6 times per day.

OTHER SAFETY INFORMATION

Tamper resistant for your protection. Use only if safety seal is intact. This product has not been clinically tested.

PURPOSE

Uses for temporary relief of:

- rash
- chills
- fatigue
- low-grade fever
- swelling
- aching or stiffness in joints or muscles associated with insect bites